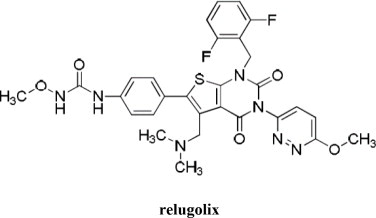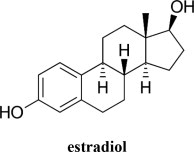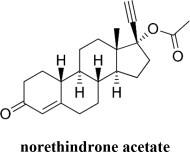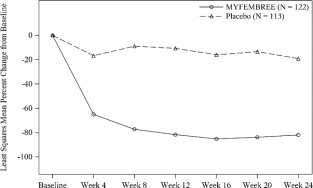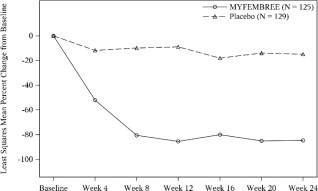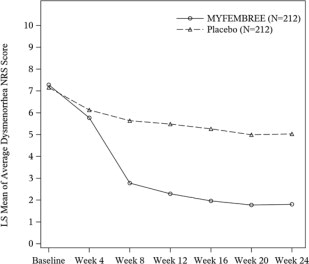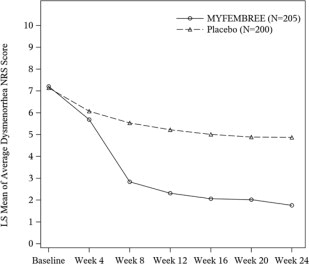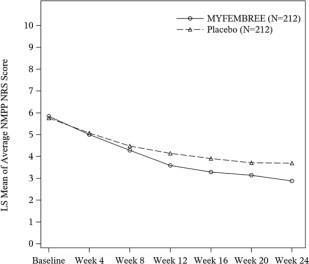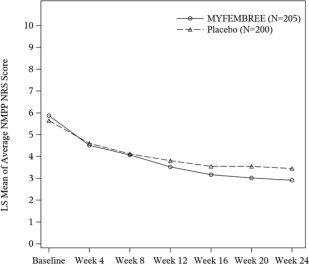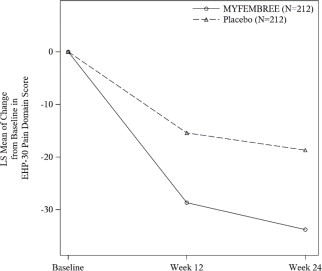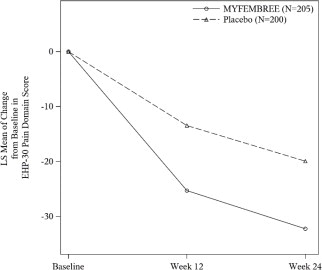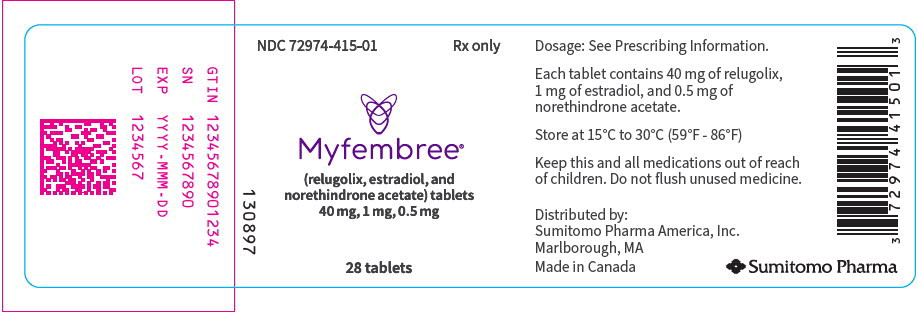 DRUG LABEL: Myfembree
NDC: 72974-415 | Form: TABLET, FILM COATED
Manufacturer: Sumitomo Pharma America, Inc
Category: prescription | Type: HUMAN PRESCRIPTION DRUG LABEL
Date: 20250904

ACTIVE INGREDIENTS: RELUGOLIX 40 mg/1 1; ESTRADIOL HEMIHYDRATE 1 mg/1 1; NORETHINDRONE ACETATE 0.5 mg/1 1
INACTIVE INGREDIENTS: MANNITOL; SODIUM STARCH GLYCOLATE TYPE A; HYDROXYPROPYL CELLULOSE, UNSPECIFIED; MAGNESIUM STEARATE; LACTOSE MONOHYDRATE; HYPROMELLOSE 2910 (6 MPA.S); TITANIUM DIOXIDE; TRIACETIN; FERRIC OXIDE YELLOW

HIGHLIGHTS OF PRESCRIBING INFORMATION

These highlights do not include all the information needed to use MYFEMBREE safely and effectively. See full prescribing information for MYFEMBREE.
MYFEMBREE® (relugolix, estradiol, and norethindrone acetate) tablets, for oral use
Initial U.S. Approval: 2021

WARNING: THROMBOEMBOLIC DISORDERS AND VASCULAR EVENTS

See full prescribing information for complete boxed warning

- Estrogen and progestin combinations, including MYFEMBREE, increase the risk of thrombotic or thromboembolic disorders, especially in women at increased risk for these events. (5.1)
- MYFEMBREE is contraindicated in women with current or a history of thrombotic or thromboembolic disorders and in women at increased risk for these events, including women over 35 years of age who smoke or women with uncontrolled hypertension. (4)

1 INDICATIONS AND USAGE

MYFEMBREE is a combination of relugolix, a gonadotropin-releasing hormone (GnRH) receptor antagonist, estradiol, an estrogen, and norethindrone acetate, a progestin, indicated in premenopausal women for the:

- management of heavy menstrual bleeding associated with uterine leiomyomas (fibroids). (1.1, 14.1)
- management of moderate to severe pain associated with endometriosis. (1.2, 14.2)

Limitations of Use

Use of MYFEMBREE should be limited to 24 months due to the risk of continued bone loss which may not be reversible. (1.3, 5.2, 6)

2 DOSAGE AND ADMINISTRATION

- Exclude pregnancy and discontinue hormonal contraceptives prior to MYFEMBREE initiation. (2.1)
- Take one tablet orally once daily. (2.2)
- Take the missed dose of MYFEMBREE as soon as possible the same day and then resume regular dosing the next day at the usual time. (2.3)
- If concomitant use of oral P-gp inhibitors is unavoidable, take MYFEMBREE at least 6 hours before taking the P-gp inhibitor (2.4)

3 DOSAGE FORMS AND STRENGTHS

Tablets: fixed-dose combination containing relugolix 40 mg, estradiol 1 mg and norethindrone acetate 0.5 mg. (3)

4 CONTRAINDICATIONS

- High risk of arterial, venous thrombotic, or thromboembolic disorder. (4)
- Pregnancy. (4)
- Known osteoporosis. (4)
- Current or history of breast cancer or other hormone-sensitive malignancies. (4)
- Known hepatic impairment or disease. (4)
- Undiagnosed abnormal uterine bleeding. (4)
- Known hypersensitivity to components of MYFEMBREE. (4)

5 WARNINGS AND PRECAUTIONS

- Thromboembolic Disorders and Vascular Events: Discontinue MYFEMBREE if an arterial or venous thrombotic, cardiovascular, or cerebrovascular event occurs. Discontinue MYFEMBREE if there is sudden unexplained partial or complete loss of vision, proptosis, diplopia, papilledema, or retinal vascular lesions and evaluate for retinal vein thrombosis immediately. (5.1)
- Bone Loss: Decreases in bone mineral density (BMD) may not be completely reversible. Baseline BMD assessment is recommended in all women. In women with heavy menstrual bleeding associated with uterine fibroids, periodic BMD assessments are recommended. In women with moderate to severe pain associated with endometriosis, annual BMD assessments are recommended. Assess risk-benefit for women with additional risk factors for bone loss. (5.2)
- Suicidal Ideation and Mood Disorders (Including Depression): Advise patients to seek medical attention for new onset or worsening depression, anxiety, or other mood changes. (5.4)
- Hepatic Impairment and Transaminase Elevations: Counsel patients on signs and symptoms of liver injury. (5.5)
- Elevated Blood Pressure: Do not use in women with uncontrolled hypertension. For women with well-controlled hypertension, continue to monitor blood pressure and stop MYFEMBREE if blood pressure rises significantly. (5.7)
- Change in Menstrual Bleeding Pattern and Reduced Ability to Recognize Pregnancy: Advise women to use non-hormonal contraception during treatment and for one week after discontinuing MYFEMBREE. MYFEMBREE may delay the ability to recognize pregnancy because it alters menstrual bleeding. Perform testing if pregnancy is suspected and discontinue MYFEMBREE if pregnancy is confirmed. (5.8)
- Risk of Early Pregnancy Loss: Can cause early pregnancy loss. Advise women to use effective non-hormonal contraception. (5.9)
- Uterine Fibroid Prolapse or Expulsion: Advise patients to seek medical attention for severe uterine bleeding. (5.10)
- Hypersensitivity Reactions: Immediately discontinue MYFEMBREE if a hypersensitivity reaction occurs. (5.14)

6 ADVERSE REACTIONS

In women with heavy menstrual bleeding associated with uterine fibroids, most common adverse reactions (incidence ≥ 3%) are vasomotor symptoms, uterine bleeding, alopecia, and decreased libido.
In women with moderate to severe pain associated with endometriosis, most common adverse reactions (incidence ≥ 3%) are headache, vasomotor symptoms, mood disorders, abnormal uterine bleeding, nausea, toothache, back pain, decreased sexual desire and arousal, arthralgia, fatigue, and dizziness. (6.1)

To report SUSPECTED ADVERSE REACTIONS, contact Sumitomo Pharma America, Inc. at 1-833-696-8268 or FDA at 1-800-FDA-1088 or www.fda.gov/medwatch.

7 DRUG INTERACTIONS

- Avoid use of MYFEMBREE with oral P-gp inhibitors. (7.1)
- Avoid use with combined P-gp and strong CYP3A inducers, as the exposure of the components of MYFEMBREE may be decreased. (7.1)

FULL PRESCRIBING INFORMATION

WARNING: THROMBOEMBOLIC DISORDERS AND VASCULAR EVENTS

- Estrogen and progestin combinations, including MYFEMBREE, increase the risk of thrombotic or thromboembolic disorders including pulmonary embolism (PE), deep vein thrombosis (DVT), stroke and myocardial infarction (MI), especially in women at increased risk for these events [see Warnings and Precautions (5.1)].
- MYFEMBREE is contraindicated in women with current or a history of thrombotic or thromboembolic disorders and in women at increased risk for these events, including women over 35 years of age who smoke or women with uncontrolled hypertension [see Contraindications (4)].

1 INDICATIONS AND USAGE

1.1 Heavy Menstrual Bleeding Associated with Uterine Leiomyomas

MYFEMBREE is indicated for the management of heavy menstrual bleeding associated with uterine leiomyomas (fibroids) in premenopausal women [see Clinical Studies (14)].

1.2 Moderate to Severe Pain Associated with Endometriosis

MYFEMBREE is indicated for the management of moderate to severe pain associated with endometriosis in premenopausal women [see Clinical Studies (14)].

1.3 Limitations of Use

Use of MYFEMBREE should be limited to 24 months due to the risk of continued bone loss that may not be reversible [see Warnings and Precautions (5.2) and Adverse Reactions (6)].

2 DOSAGE AND ADMINISTRATION

2.1 Prior to Initiation of MYFEMBREE

- Exclude pregnancy [see Contraindications (4)].
- Discontinue hormonal contraceptives [see Warnings and Precautions (5.8)].

2.2 Recommended Dosage

- Take one tablet of MYFEMBREE orally once daily at approximately the same time, with or without food [see Clinical Pharmacology (12.3)].
- Start MYFEMBREE as early as possible after the onset of menses but no later than seven days after menses has started [see Clinical Studies (14)].
- The recommended total duration of treatment with MYFEMBREE is 24 months [see Indications and Usage (1.3), Warnings and Precautions (5.2), and Adverse Reactions (6)].

2.3 Missed Dose

Take the missed dose of MYFEMBREE as soon as possible the same day and then resume regular dosing the next day at the usual time.

2.4 Dosage Modification for Concomitant Use with P-gp Inhibitors

Avoid concomitant use of MYFEMBREE with oral P-gp inhibitors. If concomitant use is unavoidable, take MYFEMBREE first and separate dosing by at least 6 hours [see Drug Interactions (7.1) and Clinical Pharmacology (12.3)].

3 DOSAGE FORMS AND STRENGTHS

Tablets: Each tablet of MYFEMBREE contains a fixed-dose combination of relugolix 40 mg, estradiol (E2) 1 mg, and norethindrone acetate (NETA) 0.5 mg. The tablets are light yellow to yellow, round, film-coated, and debossed with “MVT” on one side and “415” on the other side.

4 CONTRAINDICATIONS

MYFEMBREE is contraindicated in women:

- With a high risk of arterial, venous thrombotic, or thromboembolic disorders [see Boxed Warning and Warnings and Precautions (5.1)]. Examples include women over 35 years of age who smoke and women who are known to have:
  - current or history of deep vein thrombosis or pulmonary embolism
  - vascular disease (e.g., cerebrovascular disease, coronary artery disease, peripheral vascular disease)
  - thrombogenic valvular or thrombogenic rhythm diseases of the heart (e.g., subacute bacterial endocarditis with valvular disease, or atrial fibrillation)
  - inherited or acquired hypercoagulopathies
  - uncontrolled hypertension
  - headaches with focal neurological symptoms or migraine headaches with aura if over 35 years of age
- Who are pregnant. Exposure to MYFEMBREE early in pregnancy may increase the risk of early pregnancy loss [see Warnings and Precautions (5.9) and Use in Specific Populations (8.1)].
- With known osteoporosis, because of the risk of further bone loss [see Warnings and Precautions (5.2)].
- With current or history of breast cancer or other hormone-sensitive malignancies, and with increased risk for hormone-sensitive malignancies [see Warnings and Precautions (5.3)].
- With known hepatic impairment or disease [see Warnings and Precautions (5.5)].
- With undiagnosed abnormal uterine bleeding.
- With known anaphylactic reaction, angioedema, or hypersensitivity to MYFEMBREE or any of its components. Anaphylactoid reactions, urticaria, and angioedema have been reported [see Warnings and Precautions (5.14), Adverse Reactions (6.2)].

5 WARNINGS AND PRECAUTIONS

5.1 Thromboembolic Disorders and Vascular Events

MYFEMBREE is contraindicated in women with current or history of thrombotic or thromboembolic disorders and in women at increased risk for these events [see Contraindications (4)].

Discontinue MYFEMBREE immediately if an arterial or venous thrombotic, cardiovascular, or cerebrovascular event occurs or is suspected. Discontinue MYFEMBREE at least 4 to 6 weeks before surgery of the type associated with an increased risk of thromboembolism, or during periods of prolonged immobilization, if feasible.

Discontinue MYFEMBREE immediately if there is sudden unexplained partial or complete loss of vision, proptosis, diplopia, papilledema, or retinal vascular lesions and evaluate for retinal vein thrombosis as these have been reported in patients receiving estrogens and progestins.

Estrogen and progestin combinations, including the estradiol/norethindrone acetate component of MYFEMBREE, increase the risk of thrombotic or thromboembolic disorders, including pulmonary embolism, deep vein thrombosis, stroke, and myocardial infarction, especially in women at high risk for these events. In general, the risk is greatest among women over 35 years of age who smoke and women with uncontrolled hypertension, dyslipidemia, vascular disease, or obesity.

Two thromboembolic events (DVT and PE) occurred in one woman treated for 38 days with MYFEMBREE for moderate to severe pain associated with endometriosis.

5.2 Bone Loss

MYFEMBREE is contraindicated in women with known osteoporosis [see Contraindications (4)]. Consider the benefits and risks of MYFEMBREE treatment in patients with a history of a low trauma fracture or risk factors for osteoporosis or bone loss, including taking medications that may decrease bone mineral density (BMD) (e.g., systemic or chronic inhaled corticosteroids, anticonvulsants, or chronic use of proton pump inhibitors).

Assessment of BMD by dual-energy X-ray absorptiometry (DXA) is recommended at baseline. In women with heavy menstrual bleeding associated with uterine fibroids, periodic DXA during treatment with MYFEMBREE is recommended. In women with moderate to severe pain associated with endometriosis, annual DXA is recommended while taking MYFEMBREE. Consider discontinuing MYFEMBREE if the risk associated with bone loss exceeds the potential benefit of treatment. Although the effect of supplementation with calcium and vitamin D was not studied, such supplementation for patients with inadequate dietary intake may be beneficial. MYFEMBREE may cause a decrease in BMD in some patients. BMD loss may be greater with increasing duration of use and may not be completely reversible after stopping treatment [see Adverse Reactions (6.1)]. The impact of BMD decreases on long-term bone health and future fracture risk in premenopausal women is unknown.

5.3 Hormone-Sensitive Malignancies

MYFEMBREE is contraindicated in women with current or a history of hormone-sensitive malignancies (e.g., breast cancer) and in women at increased risk for hormone-sensitive malignancies [see Contraindications (4)]. Discontinue MYFEMBREE if a hormone-sensitive malignancy is diagnosed.

Surveillance measures in accordance with standard of care, such as breast examinations and mammography, are recommended. The use of estrogen alone or estrogen plus progestin has been reported to result in an increase in abnormal mammograms requiring further evaluation.

5.4 Suicidal Ideation and Mood Disorders (Including Depression)

Evaluate patients with a history of suicidal ideation, depression, and mood disorders prior to initiating treatment. Monitor patients for mood changes and depressive symptoms including shortly after initiating treatment, to determine whether the risks of continuing therapy with MYFEMBREE outweigh the benefits. Patients with new or worsening depression, anxiety, or other mood changes should be referred to a mental health professional, as appropriate. Advise patients to seek immediate medical attention for suicidal ideation and behavior. Re-evaluate the benefits and risks of continuing MYFEMBREE if such events occur.

Gonadotropin-releasing hormone receptor antagonists, including MYFEMBREE, have been associated with mood disorders (including depression) and suicidal ideation.

In Studies L1 and L2 in women with heavy menstrual bleeding associated with uterine fibroids, a greater proportion of women treated with MYFEMBREE compared with placebo reported depression (including depression, mood swings, and depressed mood) (2.4% vs. 0.8%), irritability (2.4% vs. 0%), and anxiety (1.2% vs. 0.8%) [see Adverse Reactions (6.1)].

In Studies S1 and S2 in women with moderate to severe pain associated with endometriosis, a greater proportion of women treated with MYFEMBREE as compared to placebo reported mood disorders (including depression) (9.1% vs. 7.2%). In addition, cases of suicidal ideation were reported with MYFEMBREE use. All women who reported suicidal ideation had a history of depression and/or anxiety [see Adverse Reactions (6.1)].

5.5 Hepatic Impairment and Transaminase Elevations

Contraindication in Patients with Hepatic Impairment

MYFEMBREE is contraindicated in patients with known hepatic impairment or disease [see Contraindications (4) and Use in Specific Populations (8.6)]. Steroid hormones may be poorly metabolized in patients with impaired liver function [see Clinical Pharmacology (12.3)].

Transaminase Elevations

Instruct women to promptly seek medical attention for symptoms or signs that may reflect liver injury, such as jaundice or right upper abdominal pain. Acute liver test abnormalities may necessitate the discontinuation of MYFEMBREE use until the liver tests return to normal and MYFEMBREE causation has been excluded.

In placebo-controlled clinical trials, in women with uterine fibroids or endometriosis, elevations (≥ 3 times the upper limit of the normal [ULN] of reference range) in alanine aminotransferase (ALT) occurred in 0.4% (1/254) and 0.7% (3/418) of MYFEMBREE-treated women, respectively, as compared to 0% (0/256) and 0.5% (2/416) of placebo-treated women, respectively; moreover, elevations (≥ 3 times ULN of reference range) in aspartate aminotransferase (AST) occurred in 0.8% (2/254) and 0.2% (1/418) of MYFEMBREE-treated women, respectively, as compared to 0.4% (1/256) and 0.5% (2/416) of placebo-treated women, respectively. No patterns in time to onset of these liver transaminase elevations were identified.

5.6 Gallbladder Disease or History of Cholestatic Jaundice

Discontinue MYFEMBREE if signs or symptoms of gallbladder disease or jaundice occur. For women with a history of cholestatic jaundice associated with past estrogen use or with pregnancy, assess the risk-benefit of continuing therapy. Studies among estrogen users suggest a small increased relative risk of developing gallbladder disease.

5.7 Elevated Blood Pressure

MYFEMBREE is contraindicated in women with uncontrolled hypertension [see Contraindications (4)]. For women with well-controlled hypertension, continue to monitor blood pressure and stop MYFEMBREE if blood pressure rises significantly.

In the placebo-controlled clinical trials in women with heavy menstrual bleeding associated with uterine fibroids or with moderate to severe pain associated with endometriosis, more women in one study (Study L1; uterine fibroids) experienced the adverse reaction of new or worsening hypertension with MYFEMBREE compared to placebo (7.0% vs. 0.8%).

5.8 Change in Menstrual Bleeding Pattern and Reduced Ability to Recognize Pregnancy

Exclude pregnancy before initiating MYFEMBREE [see Dosage and Administration (2.1)]. Start MYFEMBREE as early as possible after the start of menses but no later than 7 days after menses has started. If MYFEMBREE is initiated later in the menstrual cycle, irregular and/or heavy bleeding may initially occur. Women who take MYFEMBREE may experience amenorrhea or a reduction in the amount, intensity, or duration of menstrual bleeding, which may delay the ability to recognize pregnancy. Perform pregnancy testing if pregnancy is suspected and discontinue MYFEMBREE if pregnancy is confirmed [see Use in Specific Populations (8.1, 8.3)].

Advise women of reproductive potential to use effective non-hormonal contraception during treatment with MYFEMBREE and for one week after the final dose. Avoid concomitant use of hormonal contraceptives with MYFEMBREE. The use of estrogen-containing hormonal contraceptives can increase estrogen levels which may increase the risk of estrogen-associated adverse events and decrease the efficacy of MYFEMBREE [see Use in Specific Populations (8.1, 8.3)].

5.9 Risk of Early Pregnancy Loss

MYFEMBREE is contraindicated for use in pregnancy [see Contraindications (4)]. Based on findings from animal studies and its mechanism of action, MYFEMBREE can cause early pregnancy loss. However, in both rabbits and rats, no fetal malformations were present at any dose level tested which were associated with relugolix exposures about half and approximately 300 times exposures in women at the recommended human dose [see Use in Specific Populations (8.1)].

5.10 Uterine Fibroid Prolapse or Expulsion

Advise women with known or suspected submucosal uterine fibroids about the possibility of uterine fibroid prolapse or expulsion and instruct them to contact their physician if severe bleeding and/or cramping occurs while being treated with MYFEMBREE. In Studies L1 and L2, uterine fibroid prolapse or uterine fibroid expulsion were reported in women treated with MYFEMBREE [see Adverse Reactions (6.1)].

5.11 Alopecia

Consider discontinuing MYFEMBREE if hair loss becomes a concern [see Adverse Reactions (6.1)].

In Phase 3 placebo-controlled clinical trials in women with heavy menstrual bleeding associated with uterine fibroids, 3.5% of MYFEMBREE-treated women experienced alopecia, hair loss, and hair thinning as compared to 0.8% of placebo-treated women. In 3 of the 11 affected women treated with MYFEMBREE across Studies L1 and L2, alopecia was reported as moderate. For one MYFEMBREE-treated woman in the extension trial, alopecia was a reason for discontinuing treatment. No specific pattern of hair loss was described. The majority of affected women completed the study with reported hair loss ongoing. Whether the hair loss is reversible is unknown [see Adverse Reactions (6.1)].

5.12 Effects on Carbohydrate and Lipid Metabolism

More frequent monitoring in MYFEMBREE-treated women with prediabetes and diabetes may be necessary. MYFEMBREE may decrease glucose tolerance and result in increased blood glucose concentrations.

Monitor lipid levels and consider discontinuing MYFEMBREE if hypercholesterolemia or hypertriglyceridemia worsens. In women with pre-existing hypertriglyceridemia, estrogen therapy may be associated with elevations in triglycerides levels leading to pancreatitis. Use of MYFEMBREE is associated with increases in total cholesterol and low-density lipoprotein cholesterol (LDL-C) [see Adverse Reactions (6.1)].

5.13 Effect on Other Laboratory Results

Patients with hypothyroidism and hypoadrenalism may require higher doses of thyroid hormone or cortisol replacement therapy.

The use of estrogen and progestin combinations may raise serum concentrations of binding proteins (e.g., thyroid-binding globulin, corticosteroid-binding globulin), which may reduce free thyroid or corticosteroid hormone levels.

The use of estrogen and progestin may also affect the levels of sex hormone-binding globulin, and coagulation factors [see Clinical Pharmacology (12.2)].

5.14 Hypersensitivity Reactions

Hypersensitivity reactions, including anaphylactoid reactions, urticaria and angioedema, have been reported with MYFEMBREE [see Adverse Reactions (6.2)]. MYFEMBREE is contraindicated in women with a history of hypersensitivity reactions to relugolix or any component of MYFEMBREE [see Contraindications (4)]. Immediately discontinue MYFEMBREE if a hypersensitivity reaction occurs.

6 ADVERSE REACTIONS

The following clinically significant adverse reactions are discussed elsewhere in the labeling:

- Thromboembolic Disorders and Vascular Events [see Warnings and Precautions (5.1)]
- Bone Loss [see Warnings and Precautions (5.2)]
- Suicidal Ideation and Mood Disorders (Including Depression) [see Warnings and Precautions (5.4)]
- Hepatic Impairment and Transaminase Elevations [see Warnings and Precautions (5.5)]
- Elevated Blood Pressure [see Warnings and Precautions (5.7)]
- Change in Menstrual Bleeding Pattern and Reduced Ability to Recognize Pregnancy [see Warnings and Precautions (5.8)]
- Uterine Fibroid Prolapse or Expulsion [see Warnings and Precautions (5.10)]
- Alopecia [see Warnings and Precautions (5.11)]
- Effects on Carbohydrate and Lipid Metabolism [see Warnings and Precautions (5.12)]
- Hypersensitivity Reactions [see Warnings and Precautions (5.14)]

6.1 Clinical Trials Experience

Because clinical trials are conducted under widely varying conditions, adverse reaction rates observed in the clinical trials of a drug cannot be directly compared to rates in the clinical trials of another drug and may not reflect the rates observed in clinical practice.

Heavy Menstrual Bleeding Associated with Uterine Leiomyomas

The safety of MYFEMBREE was evaluated in two placebo-controlled clinical trials, Study L1 (LIBERTY 1) and Study L2 (LIBERTY 2), in women with heavy menstrual bleeding associated with uterine fibroids. In these trials, women received a once daily relugolix 40-mg tablet and an over-encapsulated tablet of E2 1 mg and NETA 0.5 mg (relugolix + E2/NETA), which is equivalent to 1 tablet of MYFEMBREE. Across the two trials, 254 women received MYFEMBREE once daily for 24 weeks. Additionally, 256 women received placebo for 24 weeks, and 258 women received relugolix 40-mg monotherapy once daily for 12 weeks followed by MYFEMBREE for 12 weeks [see Clinical Studies (14.1)]. Of these, 476 women were treated with MYFEMBREE in a 28-week extension trial, Study L3 (LIBERTY Extension), for a total treatment duration of up to 12 months. Demographics were similar across the studies; approximately 43% were White, 51% were Black, and approximately 23% were of Hispanic or Latino ethnicity. The mean age at study entry was approximately 42 years (range 19 to 51 years). Of women who completed Study L3, 229 were rerandomized to continue MYFEMBREE or withdraw from therapy (placebo) for an additional 52 weeks (Study L4).

Serious Adverse Reactions

In Studies L1 and L2, serious adverse reactions were reported in 3.1% of MYFEMBREE-treated women as compared to 2.3% of placebo-treated women. In MYFEMBREE-treated women, serious adverse drug reactions included uterine myoma expulsion and menorrhagia experienced by one woman and uterine leiomyoma (prolapse), cholecystitis, and pelvic pain reported for one woman each.

Adverse Reactions Leading to Study Drug Discontinuation

In Studies L1 and L2, 3.9% of women treated with MYFEMBREE discontinued therapy due to adverse reactions, as compared to 4.3% receiving placebo. The most common adverse reaction leading to discontinuation of MYFEMBREE was uterine bleeding (1.2%) with an onset usually reported within the first 3 months of therapy.

Common Adverse Reactions

The most common adverse reactions reported in at least 3% of women treated with MYFEMBREE for heavy menstrual bleeding associated with uterine fibroids and at an incidence greater than placebo during double-blind placebo-controlled treatment are summarized below in Table 1.

Table 1: Adverse Reactions Occurring in 3% or More in Women with Heavy Menstrual Bleeding Associated with Uterine Fibroids Treated with MYFEMBREE in Studies L1 and L2
Adverse Reaction | MYFEMBREE (N = 254) % | Placebo (N = 256) %
Vasomotor symptoms^1 | 10.6 | 6.6
Abnormal uterine bleeding^2 | 6.3 | 1.2
Alopecia | 3.5 | 0.8
Libido decreased^3 | 3.1 | 0.4
^1 Includes hot flush, hyperhidrosis, or night sweats.
^2 Includes menorrhagia, metrorrhagia, vaginal hemorrhage, polymenorrhea, and menstruation irregular.
^3 Includes libido decreased and loss of libido.

In Study L1, more women experienced the adverse reaction of new or worsening hypertension with MYFEMBREE as compared to placebo (7.0% vs. 0.8%).

The most common adverse reactions reported during the extension trial, Study L3, were similar to those reported in the placebo-controlled trials.

Less Common Adverse Reactions

Adverse reactions reported in at least 2% and less than 3% of women with heavy menstrual bleeding associated with uterine fibroids in the MYFEMBREE treated group and greater incidence than placebo included irritability, dyspepsia, and breast cyst. Other important adverse reactions reported in MYFEMBREE-treated women included one serious reaction each of uterine myoma expulsion (0.4%) and uterine leiomyoma (prolapse) (0.4%).

Bone Loss

The effect of MYFEMBREE on BMD was assessed by DXA. The least squares mean percent changes from baseline in lumbar spine BMD at Month 6 in Studies L1 and L2 are presented below in Table 2.

Table 2: Mean Percent Change (On-Treatment) from Baseline in Lumbar Spine BMD in Women with Heavy Menstrual Bleeding Associated with Uterine Fibroids in Studies L1 and L2 at Month 6
 | MYFEMBREE | Placebo
Number of subjects | 254 | 256
Percent change from baseline (95% CI) | -0.23 (-0.64, 0.18) | 0.18 (-0.21, 0.58)
Treatment difference, % | -0.42
Abbreviations: BMD = bone mineral density; CI = confidence interval.

In the open-label extension trial, Study L3, women received an additional 28 weeks of MYFEMBREE for a total of up to 52 weeks of treatment. Women from Study L3 showed continued bone loss at Months 6 and 12 when treated with up to 52 weeks of MYFEMBREE. The least squares mean percent changes from baseline in lumbar spine BMD at Months 6 and 12 are presented below in Table 3.

Table 3: Mean Percent Change (On-Treatment) from Baseline* in Lumbar Spine BMD at Month 6* and Month 12 for MYFEMBREE-Treated Women with Heavy Menstrual Bleeding Associated with Uterine Fibroids in Study L3
 | Number of Women (N = 163)
 | Month 6* | Month 12
Percent change from baseline* (95% CI) | -0.23 (-0.69, 0.24) | -0.80 (-1.36, -0.25)
Abbreviations: BMD = bone mineral density; CI = confidence interval.
* Baseline and Month 6 assessments include only those participants from Studies L1 and L2 who participated in Study L3.

A separate concurrent prospective observational study enrolled 262 women with heavy menstrual bleeding associated with uterine fibroids who were age-matched to participants of Studies L1 and L2. While these women were not randomized to receive treatment for heavy menstrual bleeding associated with uterine fibroids, women were permitted to receive treatment from their provider during the clinical trials for this indication. Women underwent DXA scans at baseline, Month 6 and Month 12 to monitor for changes in BMD. The mean percent changes from baseline (95% CI) in lumbar spine BMD at Months 6 and 12 were 0.00 (-0.32, 0.31) and -0.41 (-0.77, -0.05), respectively.

A decline in lumbar spine BMD of > 3% was observed in 23% (30/132) of women who had a DXA scan following 12 months of MYFEMBREE treatment in Study L3 and in 17.4% (37/213) of untreated women in the Observational Uterine Fibroids Cohort. A decline of > 8% was seen in 0.8% (1/132) of women treated with MYFEMBREE who completed a DXA scan at Month 12 and in 0.9% (2/213) of untreated women in the Observational Uterine Fibroids Cohort.

In Studies L1, L2, and L3, four of women treated with MYFEMBREE experienced low trauma fractures (defined as a fall from standing height or less). Two women, one from Study L1 and one from Study L2, fractured after 117 and 166 days of treatment with MYFEMBREE. Two women in Study L3, both treated with relugolix monotherapy for 12 weeks prior to MYFEMBREE therapy, fractured after 149 and 164 days of treatment with MYFEMBREE.

Depression, Mood Disorders, and Suicidal Ideation

In Studies L1 and L2, MYFEMBREE was associated with adverse mood changes. A greater proportion of women treated with MYFEMBREE compared to placebo reported depression (including depression, mood swings, and depressed mood) (2.4% vs. 0.8%), irritability (2.4% vs. 0%), and anxiety (1.2% vs. 0.8%).

Resumption of Menstruation after Discontinuation

Post study menstrual status was available for 35 women in Study L1 and 30 women in Study L2 who were treated with MYFEMBREE and prematurely discontinued the study or did not continue into the long-term extension study. For these women, 100% (35/35) in Study L1 and 93.3% (28/30) in Study L2 resumed menses. The mean time from last dose to occurrence of menses was 36 days in Study L1 and 30.7 days in Study L2. Mean time to occurrence of menses was longer for women who achieved amenorrhea (40.6 days and 41.1 days in Studies L1 and L2, respectively) compared with women without amenorrhea (33.0 days and 26.6 days in Studies L1 and L2, respectively) in the last 35 days of treatment. After 12 months of treatment with MYFEMBREE (Study L1 or Study L2, then Study L3) 93.8% (61/65) of women resumed menses. Mean time from last dose of drug to occurrence of menses was 40.5 days. Mean time to occurrence of menses was longer in women who reported amenorrhea over the last 35 days of treatment compared with women without amenorrhea over the last 35 days of treatment (45.6 days vs. 32.6 days, respectively).

Women who did not have a return to menses included those who had surgery, used alternative medications associated with amenorrhea, entered menopause, and unknown cause.

Increases in Lipids

Lipid levels were assessed at baseline and Week 24/End of Treatment in Studies L1 and L2. Among women with normal total cholesterol (< 200 mg/dL) at baseline, increases to 200 to < 240 mg/dL were seen in 13.7% of women treated with MYFEMBREE as compared to 7.7% of women treated with placebo, and increases to ≥ 240 mg/dL were seen in 1.7% and 0.6% of MYFEMBREE- and placebo-treated women, respectively. For women with LDL < 130 mg/dL at baseline, increases to 130 to < 160 mg/dL, 160 to < 190 mg/dL and ≥ 190 mg/dL were seen in 9.3%, 1.5%, and 0.5% of women treated with MYFEMBREE as compared to 6.5%, 0.5% and 0% of women treated with placebo, respectively.

Moderate to Severe Pain Associated with Endometriosis

The safety of MYFEMBREE was evaluated in two placebo-controlled clinical trials, Study S1 and Study S2, in women with moderate to severe pain associated with endometriosis. In these trials, women received once daily one relugolix 40-mg tablet with one over-encapsulated tablet of E2 1 mg and NETA 0.5 mg (relugolix + E2/NETA), which is equivalent to one tablet of MYFEMBREE. Across the two trials, 418 women received MYFEMBREE once daily for 24 weeks, 416 women received placebo for 24 weeks, and 417 women received relugolix 40 mg monotherapy once daily for 12 weeks followed by MYFEMBREE for 12 weeks [see Clinical Studies (14)]. Of these, 799 women were treated with MYFEMBREE in an 80-week extension trial, Study S3, for a total treatment duration of up to 24 months. Demographics were similar across these trials; 91% were white, 6% were Black, and 12% were of Hispanic or Latino ethnicity. The mean age at study entry was 34 years (range 18 to 50 years).

Serious Adverse Reactions

In Studies S1 and S2, serious adverse reactions were reported in 2.9% of MYFEMBREE-treated women as compared to 2.2% of placebo-treated women. In MYFEMBREE-treated women, serious adverse reactions included uterine hemorrhage, suicidal ideation, cholelithiasis, and cholecystitis.

Adverse Reactions Leading to Study Drug Discontinuation

In Studies S1 and S2, 4.5% of MYFEMBREE-treated women discontinued therapy due to adverse reactions as compared to 2.9% of placebo-treated women. The most common adverse reaction (1.7%) leading to discontinuation in MYFEMBREE-treated women was mood-related disorders (including depression, mood swings, altered mood, affect lability, and suicidal ideation).

Common Adverse Reactions

The most common adverse reactions reported in at least 3% of women treated with MYFEMBREE for moderate to severe pain associated with endometriosis and with an incidence greater than placebo during Studies S1 and S2 are summarized below in Table 4.

Table 4: Adverse Reactions Occurring in 3% or More of Women with Moderate to Severe Pain Associated with Endometriosis Treated with MYFEMBREE
Adverse Reaction | MYFEMBREE (N = 418) % | Placebo (N = 416) %
Headache | 33.0 | 26.4
Vasomotor symptoms^1 | 13.2 | 7.2
Mood disorders^2 | 9.1 | 7.2
Abnormal uterine bleeding^3 | 6.7 | 4.6
Nausea | 6.0 | 4.1
Toothache | 5.5 | 2.4
Back pain | 4.8 | 2.9
Decreased sexual desire and arousal^4 | 4.3 | 1.2
Arthralgia | 3.6 | 2.2
Fatigue | 3.1 | 2.4
Dizziness | 3.1 | 1.2
^1 Includes hot flush, hyperhidrosis, night sweats, and flushing.
^2 Includes affect lability, affective disorder, anxiety, depressed mood, depression, emotional distress, generalized anxiety disorder, irritability, mixed anxiety and depressive disorder, mood altered, mood swings, and suicidal ideation.
^3 Includes menorrhagia, metrorrhagia, vaginal hemorrhage, uterine hemorrhage, polymenorrhea, and menstruation irregular.
^4 Includes libido decreased, libido disorder, and female sexual arousal disorder.

The most common adverse reactions reported in the safety extension trial, Study S3, were similar to those reported in the placebo-controlled trials.

Less Common Adverse Reactions

Adverse reactions reported in at least 2% and less than 3% of women with moderate to severe pain associated with endometriosis in the MYFEMBREE group and with a greater incidence than placebo included diarrhea (2.4%), peripheral edema (2.2%), and vulvovaginal dryness (2.2%).

Bone Loss

The effect of MYFEMBREE on BMD was assessed by DXA. The least squares (LS) mean percent changes from baseline in lumbar spine BMD at Month 6 and for women with moderate to severe pain associated with endometriosis in Studies S1 and S2 are presented in Table 5.

Table 5: LS Mean Percent Change (On-Treatment) from Baseline in Lumbar Spine BMD in Women with Moderate to Severe Pain Associated with Endometriosis at Month 6 in Studies S1 and S2
 | Treatment Month 6
 | MYFEMBREE | Placebo
Number of subjects | 418 | 416
Percent change from baseline (95% CI) | -0.72 (-1.06, -0.38) | 0.12 (-0.22, 0.47)
Treatment difference, % | -0.84
Abbreviations: LS = least squares; BMD = bone mineral density; CI = confidence interval.

In the open-label extension, Study S3, women received an additional 80 weeks of MYFEMBREE for a total of up to 24 months of treatment. The least squares (LS) mean percent changes from baseline in lumbar spine BMD at Months 6, 12, and 24 for women treated with MYFEMBREE in Studies S1 and S2 and then continued MYFEMBREE for an additional 80 weeks in Study S3 are presented below in Table 6.

Table 6: LS Mean Percent Change (On-Treatment) from Baseline* in Lumbar Spine BMD at Months 6*, 12, and 24 for Women with Moderate to Severe Pain Associated with Endometriosis Treated with MYFEMBREE in Study S3
 | Number of Women (N = 277)
 | Month 6* (n=264) | Month 12 (n=228) | Month 24 (n=163)
Percent change from baseline* (95% CI) | -0.91 (-1.30, -0.53) | -0.81 (-1.26, -0.36) | -0.45 (-1.03, 0.13)
Abbreviations: LS = least squares; BMD = bone mineral density; CI = confidence interval; N = number of subjects who received continuous MYFEMBREE treatment throughout Studies S1/S2 and S3; n = number of subjects who had BMD assessments.
* Baseline and Month 6 assessments include only those participants from Studies S1 and S2 who also participated in Study S3.

Changes in bone mineral density with MYFEMBREE treatment beyond 24 months have not been elucidated.

A separate concurrent prospective observational study enrolled 452 women with moderate to severe pain associated with endometriosis who were age-matched to participants of Studies S1 and S2. While these women were not randomized to receive treatment for moderate to severe pain associated with endometriosis, women were permitted to receive treatment from their provider for this indication. Women underwent DXA scans at baseline and Months 6 and 12 to monitor for changes in BMD. The mean percent changes from baseline (95% CI) in lumbar spine BMD at Months 6 and 12 were 0.35 (0.13, 0.57) and 0.53 (0.24, 0.83), respectively.

In women with moderate to severe pain associated with endometriosis, a decline in lumbar spine BMD of > 3% from pre-treatment baseline was observed in 19.7% (45/228) of women who had a DXA scan following 12 months of MYFEMBREE treatment in Study S3 and in 9.1% (29/320) of untreated women in the Observational Endometriosis Cohort. A decline of > 7% to ≤ 8% from pre-treatment baseline was seen in 0.9% (2/228) of women treated with MYFEMBREE who completed a DXA scan at Month 12 in Study S3 and in 0.6% (2/320) of untreated women in the Observational Endometriosis Cohort.

Following 24 months of MYFEMBREE treatment in Study S3, a decline in lumbar spine BMD of > 3% from pre-treatment baseline occurred in 20.2% (33/163) of women and a decline of > 7% from pre-treatment baseline occurred in 2.5% (4/163) of women. At the femoral neck, a decline in BMD of >7% was observed in 1.8% (3/163) women, one of whom (0.6%) also had a decline in BMD of > 7% at the total hip. The maximum percent decline from pre-treatment baseline at the lumbar spine, femoral neck and total hip at Month 24 was 9.1%, 8.8% and 7.0%, respectively.

BMD loss may not be completely reversible after stopping treatment.

In Study S3, two women sustained fractures after falling. One woman, who was treated for almost 24 weeks with MYFEMBREE following 12 weeks of relugolix monotherapy, sustained a tibia/fibula fracture and one who was treated for 104 weeks with MYFEMBREE, sustained a wrist fracture 144 days after she discontinued MYFEMBREE. The impact of BMD loss on long-term bone health and future fracture risk in premenopausal women is unknown.

Suicidal Ideation and Mood Disorders (Including Depression)

In Studies S1 and S2, a greater proportion of women treated with MYFEMBREE compared with placebo reported mood disorders (including depression) (9.1% vs. 7.2%).

In addition, cases of suicidal ideation were reported in the safety extension trial, Study S3.

Resumption of Menstruation after Discontinuation

Post-study menstrual status was available for 55 women in Study S1 and 59 women in Study S2 who were treated with MYFEMBREE and either prematurely discontinued the study or did not continue into the extension study. For these women, 83.6% (46/55) in Study S1 and 84.7% (50/59) in Study S2 resumed menses. The mean time from last dose to occurrence of menses was 27.1 days in Study S1 and 39.2 days in Study S2. Mean time to occurrence of menses was longer for women who achieved amenorrhea (34.3 days and 42.8 days in Studies S1 and S2, respectively) compared with women without amenorrhea (21.0 days and 32.1 days in Studies S1 and S2, respectively) in the last 28 days of treatment. After 12 months of treatment with MYFEMBREE (Study S1 or Study S2, then Study S3), 97.9% (46/47) of women resumed menses. Mean time from last dose of drug to occurrence of menses was 36.7 days.

Women who did not have a return to menses included those who had surgery, used alternative medications associated with amenorrhea, or became pregnant.

Increases in Lipids

Lipid levels were assessed at baseline and Week 24/End of Treatment in Studies S1 and S2. Among women with normal total cholesterol (< 200 mg/dL) at baseline, increases to ≥ 200 to < 240 mg/dL were seen in 13.6% (41/302) of MYFEMBREE- treated women as compared to 9.3% (27/289) of placebo-treated women, and increases to ≥ 240 mg/dL were seen in 0.7% (2/302) of MYFEMBREE-treated women as compared to 1.0% (3/289) of placebo-treated women. For women with LDL < 130 mg/dL at baseline, increases to 130 to < 160 mg/dL, 160 to < 190 mg/dL and ≥ 190 mg/dL were seen in 8.0%, 0.3%, and 0% of MYFEMBREE-treated women as compared to 7.6%, 0% and 0% of placebo-treated women. Among women with normal HDL at baseline (≥ 60 mg/dL), declines to 40 to < 60 mg/dL occurred in 22.2% (49/221) of MYFEMBREE-treated women as compared to 12.2% (27/221) of placebo-treated women.

6.2 Postmarketing Experience

The following adverse reactions have been identified during post-approval use of MYFEMBREE, as well as post-approval use of relugolix monotherapy outside of the United States. Because these reactions are reported voluntarily from a population of uncertain size, it is not always possible to reliably estimate their frequency or establish a causal relationship to drug exposure.

Immune system disorders: anaphylactoid reaction

Skin and subcutaneous tissue disorders: drug eruption, angioedema, urticaria

Neoplasms (benign, malignant, and unspecified): uterine leiomyoma degeneration

7 DRUG INTERACTIONS

7.1 Effect of Other Drugs on MYFEMBREE

P-gp Inhibitors

Co-administration of MYFEMBREE with P-gp inhibitors increases the AUC and maximum concentration (Cmax) of relugolix [see Clinical Pharmacology (12.3)] and may increase the risk of adverse reactions associated with MYFEMBREE. Avoid use of MYFEMBREE with oral P-gp inhibitors.

If use is unavoidable, take MYFEMBREE first, separate dosing by at least 6 hours, and monitor patients for adverse reactions [see Dosage and Administration (2.4)].

Combined P-gp and Strong CYP3A Inducers

Use of MYFEMBREE with combined P-gp and strong CYP3A inducers decreases the AUC and Cmax of relugolix, estradiol, and/or norethindrone [see Clinical Pharmacology (12.3)] and may decrease the therapeutic effects of MYFEMBREE. Avoid use of MYFEMBREE with combined P-gp and strong CYP3A inducers.

8 USE IN SPECIFIC POPULATIONS

8.1 Pregnancy

Pregnancy Exposure Registry

There is a pregnancy exposure registry that monitors pregnancy outcomes in women exposed to MYFEMBREE during pregnancy. Pregnant females exposed to MYFEMBREE and healthcare providers are encouraged to call the MYFEMBREE Pregnancy Exposure Registry at 1-855-428-0707.

Risk Summary

MYFEMBREE is contraindicated in pregnancy [see Contraindications (4) and Warnings and Precautions (5.9)]. Based on findings from animal studies and its mechanism of action, MYFEMBREE may cause early pregnancy loss. Discontinue MYFEMBREE if pregnancy occurs during treatment [see Warnings and Precautions (5.9) and Clinical Pharmacology (12.1)].

The limited human data with the use of MYFEMBREE in pregnant women are insufficient to evaluate for a drug-associated risk of major birth defects, miscarriage, or adverse maternal or fetal outcomes [see Data].

In animal reproduction studies, oral administration of relugolix in pregnant rabbits during organogenesis resulted in spontaneous abortion and total litter loss at relugolix exposures about half those at the maximum recommended human dose (MRHD) of 40 mg. In both rabbits and rats, no fetal malformations were present at any dose level tested which were associated with relugolix exposures about half and approximately 300 times exposures in women at the MRHD, respectively [see Data].

Epidemiologic studies and meta-analyses have not found an increased risk of genital or non-genital birth defects (including cardiac anomalies and limb-reduction defects) following exposure to estrogens and progestins before conception or during early pregnancy.

The estimated background risk of major birth defects and miscarriage for the indicated population is unknown. There are insufficient data to conclude whether the presence of uterine fibroids or endometriosis reduces the likelihood of achieving pregnancy or increases the risk of adverse pregnancy outcomes. All pregnancies have a background risk of birth defect, loss, or other adverse outcomes. In the United States general population, the estimated background risks of major birth defects and miscarriage in clinically recognized pregnancies are 2% to 4% and 15% to 20%, respectively.

Data

Animal Data

In an embryo-fetal development study, oral administration of relugolix to pregnant rabbits during the period of organogenesis (Days 6 to 18 of gestation) resulted in abortion, total litter loss, or decreased number of live fetuses at a dose of 9 mg/kg/day (about half the human exposure at the maximum recommended human dose [MRHD] of 40 mg daily, based on AUC). No treatment related malformations were observed in surviving fetuses. No treatment related effects were observed at 3 mg/kg/day (about 0.1-fold the MRHD) or lower. The binding affinity of relugolix for rabbit GnRH receptors is unknown.

In a similar embryo-fetal development study, oral administration of relugolix to pregnant rats during the period of organogenesis (Days 6 to 17 of gestation) did not affect pregnancy status or fetal endpoints at doses up to 1000 mg/kg/day (300 times the MRHD), a dose at which maternal toxicity (decreased body weight gain and food consumption) was observed. A no observed adverse effect level (NOAEL) for maternal toxicity was 200 mg/kg/day (86 times the MRHD). In rats, the binding affinity of relugolix for GnRH receptors is more than 1000-fold lower than that in humans, and this study represents an assessment of non-pharmacological targets of relugolix during pregnancy. No treatment related malformations were observed up to 1000 mg/kg/day.

In a pre- and postnatal developmental study in pregnant and lactating rats, oral administration of relugolix to rats during late pregnancy and lactation (Day 6 of gestation to Day 20 of lactation) had no effects on pre- and postnatal development at doses up to 1000 mg/kg/day (300 times the MRHD), a dose in which maternal toxicity was observed (effects on body weight gain). A NOAEL for maternal toxicity was 100 mg/kg/day (34 times the MRHD).

8.2 Lactation

Risk Summary

Detectable amounts of estrogen and progestin have been identified in the breast milk of women receiving estrogen plus progestin therapy and can reduce milk production in breast-feeding women. This reduction can occur at any time but is less likely to occur once breast-feeding is well established.

Relugolix was detected in human breast milk. In a single dose milk-only lactation study in 8 healthy adult lactating women, the mean total amount of relugolix recovered in human breast milk over the first 24 hours was 0.0031 mg and over 120 hours (5 days) was 0.0042 mg following a single, oral, maternal dose of 40 mg. The mean calculated daily infant dose was 0.0006 mg/kg/day using 0.0031mg (the amount recovered in human breast milk over the first 24 hours). The relative infant dose was 0.105% of the maternal weight-adjusted dose of 40 mg.

There are no data on the effects of relugolix or its metabolites on the breastfed child, or the effects on milk production.

The developmental and health benefits of breast-feeding should be considered along with the mother's clinical need for MYFEMBREE and any potential adverse effects on the breastfed child from MYFEMBREE or from the underlying maternal condition.

8.3 Females and Males of Reproductive Potential

Based on animal data and the mechanism of action, MYFEMBREE can cause early pregnancy loss if MYFEMBREE is administered to pregnant women [see Use in Specific Populations (8.1)].

Pregnancy Testing

MYFEMBREE may delay the ability to recognize pregnancy because it may reduce the intensity, duration, and amount of menstrual bleeding [see Warnings and Precautions (5.8)]. Exclude pregnancy before initiating treatment with MYFEMBREE. Perform pregnancy testing if pregnancy is suspected during treatment with MYFEMBREE and discontinue treatment if pregnancy is confirmed [see Contraindications (4) and Warnings and Precautions (5.8)].

Contraception

Advise women of reproductive potential to use effective non-hormonal contraception during treatment with MYFEMBREE and for at least 1 week following discontinuation. Avoid concomitant use of hormonal contraceptives with MYFEMBREE. The use of estrogen-containing hormonal contraceptives may increase the risk of estrogen-associated adverse events and is expected to decrease the efficacy of MYFEMBREE [see Warnings and Precautions (5.8)].

8.4 Pediatric Use

Safety and effectiveness of MYFEMBREE in pediatric patients have not been established.

8.6 Hepatic Impairment

MYFEMBREE is contraindicated in women with hepatic impairment or disease [see Contraindications (4)]. The use of E2 (a component of MYFEMBREE) in patients with hepatic impairment is expected to increase the exposure to E2 and increase the risk of E2-associated adverse reactions [see Clinical Pharmacology (12.3)].

10 OVERDOSAGE

Overdosage of estrogen plus progestin may cause nausea, vomiting, breast tenderness, abdominal pain, drowsiness, fatigue, and withdrawal bleeding.

Supportive care is recommended if an overdose occurs. The amount of relugolix, estradiol, or norethindrone removed by hemodialysis is unknown.

11 DESCRIPTION

MYFEMBREE tablets for oral administration contain a fixed-dose combination of relugolix 40 mg, estradiol 1 mg, and norethindrone acetate 0.5 mg as active ingredients.

Relugolix is a non-peptide small molecule, GnRH receptor antagonist. It is a white to off white to slightly yellow solid and is sparingly soluble in water. The chemical name is N-(4-{1-[(2,6-difluorophenyl)methyl]-5-[(dimethylamino)methyl]-3-(6-methoxypyridazin-3-yl)-2,4-dioxo-1,2,3,4-tetrahydrothieno[2,3-d]pyrimidin-6-yl}phenyl)-N-methoxyurea with the empirical formula of C29H27F2N7O5S and a molecular weight of 623.63. The structural formula is:

Estradiol (E2), an estrogen, is present as the hemihydrate (C18H24O2•½H2O) which is a white or almost white crystalline powder. Its chemical name is estra-1, 3, 5 (10)-triene-3, 17β-diol with the empirical formula of C18H24O2 and a molecular weight of 272.4. The structural formula is:

Norethindrone acetate (NETA), a progestin, is a white or yellowish-white crystalline powder. Its chemical name is 17-Hydroxy-19-nor-17α-pregn-4-en-20-yn-3-one acetate with the empirical formula of C22H28O3 and a molecular weight of 340.5. The structural formula is:

Each MYFEMBREE (relugolix, estradiol, and norethindrone acetate) film-coated tablet contains the following inactive ingredients: hydroxypropyl cellulose, hypromellose, iron oxide yellow, lactose monohydrate, mannitol, magnesium stearate, sodium starch glycolate, titanium dioxide, and triacetin.

12 CLINICAL PHARMACOLOGY

12.1 Mechanism of Action

MYFEMBREE is a combination of relugolix, estradiol (E2), and norethindrone acetate (NETA).

Relugolix is a non-peptide GnRH receptor antagonist that competitively binds to pituitary GnRH receptors, thereby reducing the release of luteinizing hormone (LH) and follicle-stimulating hormone (FSH), leading to decreased serum concentrations of the ovarian sex hormones estradiol and progesterone and reduced bleeding associated with uterine fibroids and pain associated with endometriosis.

Estradiol acts by binding to nuclear receptors that are expressed in estrogen-responsive tissues. As a component of MYFEMBREE, the addition of exogenous estradiol may reduce the increase in bone resorption and resultant bone loss that can occur due to a decrease in circulating estrogen concentrations from relugolix alone.

Progestins such as norethindrone act by binding to nuclear receptors that are expressed in progesterone-responsive tissues. As a component of MYFEMBREE, norethindrone may protect the uterus from the potential adverse endometrial effects of unopposed estrogen.

12.2 Pharmacodynamics

Estradiol and norethindrone acetate (components of MYFEMBREE) may have the following effects:

- Increased thyroxin-binding globulin levels leading to [see Warnings and Precautions (5.13)]:
  - Increased circulating total thyroid hormone concentrations as measured by protein-bound iodine (PBI), thyroxine (T4) levels (by column or by radioimmunoassay), or triiodothyronine (T3) concentrations by radioimmunoassay
  - Decreased T3 resin uptake
  - Unaltered free T4 and free T3 concentrations in women with normal thyroid function [see Warnings and Precautions (5.13)].
- Elevated corticosteroid-binding globulin (CBG) and sex hormone-binding globulin (SHBG) concentrations leading to increases in total circulating corticosteroid and sex hormone concentrations, respectively [see Warnings and Precautions (5.13)].
- Possible decreased free testosterone concentrations.
- Possible increased other plasma proteins concentrations (angiotensinogen/renin substrate, alpha-1 antitrypsin, ceruloplasmin).
- Increased plasma high-density lipoprotein (HDL) and HDL2 cholesterol subfraction concentration, reduced low-density lipoprotein concentration, increased triglyceride concentrations.
- Accelerated prothrombin time, partial thromboplastin time, and platelet aggregation time; increased platelet count; increased factors II, VII antigen, VIII coagulant activity, IX, X, XII, VII-X complex, and beta-thromboglobulin; decreased concentrations of anti-factor Xa and antithrombin III, decreased antithrombin III activity, increased concentrations of fibrinogen and fibrinogen activity; increased plasminogen antigen and activity.

Cardiac Electrophysiology

At a dose 9 times the maximum approved recommended dose of relugolix, the QT interval was not prolonged to a clinically relevant extent.

The effect of estradiol and norethindrone acetate (two of the components of MYFEMBREE) on the QTc interval has not been studied.

12.3 Pharmacokinetics

The pharmacokinetic parameters of relugolix, unconjugated estradiol, and norethindrone after administration of a single dose of MYFEMBREE to healthy postmenopausal women under fasted conditions are summarized in Table 7.

Table 7: Pharmacokinetic Parameters of Relugolix, Unconjugated Estradiol, and Norethindrone After Single Dose Administration of MYFEMBREE
 | Relugolix | Unconjugated Estradiol | Norethindrone
AUC0-inf (ng·hr/mL or pg·hr/mL), mean (SD) | 198.1 (111.6) | 818.7 (334.4) | 17.5 (8.5)
Cmax (ng/mL or pg/mL), mean (SD) | 26.0 (18.2) | 28.0 (19.2) | 3.6 (1.4)
Tmax (hr), median (min, max) | 2.00 (0.25, 5.00) | 7.00 (0.25, 24.00) | 1.0 (0.50, 4.00)
Abbreviations: AUC = area under the concentration-time curve; AUC0-inf = AUC from time 0 extrapolated to infinity; Cmax = maximum observed concentration; E2 = estradiol; NET = norethindrone; Tmax = time to maximum observed concentration.
Notes: AUC0-inf is presented in ng·hr/mL for relugolix, NET and in pg·hr/mL for unconjugated E2. Cmax is presented in ng/mL for relugolix, NET and in pg/mL for unconjugated E2.

Relugolix exhibits greater than dose-proportional exposures at doses ranging from 1 mg to 80 mg (0.025 to 2 times the approved recommended dose) and approximately dose-proportional exposures at doses ranging from 80 mg to 360 mg (2 to 9 times the approved recommended dose). Relugolix concentrations reach steady-state within 12 days, and the degree of accumulation is approximately 2-fold, upon once daily administration.

Estradiol and norethindrone concentrations reach steady-state within 2 weeks, with an accumulation of 33% to 47% above concentrations seen after administration of a single dose, upon once daily administration.

Absorption

The mean (%CV) absolute bioavailability of relugolix is 12% (62%).

Effect of Food

The AUC0-inf and Cmax of relugolix decreased by 38% and 55%, respectively, after administration of MYFEMBREE following consumption of a high-fat, high-calorie meal (i.e., 800-1000 calorie meal in which 50% of calories are derived from fat) compared with the fasted state; however, the decrease in exposure to relugolix is considered not to be clinically meaningful. No clinically meaningful effects of food on the exposure to estradiol or norethindrone were observed.

Distribution

Plasma protein binding of relugolix is 68% to 71%, primarily to albumin and to a lesser extent to α1-acid glycoprotein. The mean blood-to-plasma ratio is 0.78. Estradiol circulates in the blood bound to SHBG (36% to 37%) and to albumin (61%), while only approximately 1% to 2% is unbound. Norethindrone also binds to a similar extent to SHBG (36%) and to albumin (61%).

Elimination

After administration of a single dose of MYFEMBREE, the mean (SD) terminal phase elimination half-life (t1/2) of relugolix, estradiol, and norethindrone are 61.5 (13.2) hours, 16.6 (7.7) hours, and 10.9 (3.1) hours, respectively.

Metabolism

Relugolix is metabolized primarily by CYP3A and to a lesser extent by CYP2C8 in vitro.

Estradiol is converted reversibly to estrone, and both can be converted to estriol, which is a major urinary metabolite. Estrogens also undergo enterohepatic recirculation due to sulfate and glucuronide conjugation in the liver, biliary secretion of conjugates into the intestine, and hydrolysis in the intestine followed by reabsorption.

Norethindrone undergoes extensive biotransformation, primarily by reduction, in addition to sulfation, glucuronidation, and oxidation, respectively, by sulfotransferases (SULTs), glucuronosyltransferases (UGTs), and CYP enzymes, including CYP3A4. The majority of metabolites in the circulation are sulfates, with glucuronides accounting for most of the urinary metabolites.

Excretion

After oral administration of a single 80 mg radiolabeled dose of relugolix, approximately 81% of the radioactivity was recovered in feces (4.2% as unchanged) and 4.1% in urine (2.2% as unchanged).

Estradiol is excreted in the urine as glucuronide and sulfate conjugates. Norethindrone is primarily excreted in urine as various polar metabolites.

Specific Populations

No clinically significant differences in the pharmacokinetics of relugolix were observed based on age (19 to 53 years), race/ethnicity (Asian [49%], White [24%], Black/African American [24%]), body weight (38 to 144 kg), mild to severe renal impairment (creatinine clearance [CLcr] 15 to 89 mL/min, as estimated by the Cockcroft-Gault equation), or mild or moderate hepatic impairment (Child-Pugh A or B). The effects of severe hepatic impairment (Child-Pugh C) or end-stage renal disease with or without hemodialysis on the pharmacokinetics of relugolix have not been studied.

The effects of renal or hepatic impairment on the pharmacokinetics of estradiol or norethindrone have not been studied. However, estradiol blood concentrations are expected to be increased in patients with hepatic impairment compared to patients with normal hepatic function.

Drug Interaction Studies

Clinical Studies

- Combined P-gp and Moderate CYP3A Inhibitor: Co-administration of MYFEMBREE with erythromycin (P-gp and moderate CYP3A inhibitor) increased the AUC and Cmax of relugolix by 4.1-fold and 3.8- fold, respectively. No clinically meaningful differences in the pharmacokinetics of unconjugated estradiol, total estrone, unconjugated estrone, and norethindrone were observed.
- Combined P-gp and Strong CYP3A Inducer: Co-administration with rifampin (P-gp and strong CYP3A inducer) decreased the AUC and Cmax of relugolix by 55% and 23%, respectively.
- Other Drugs: No clinically significant differences in the pharmacokinetics of relugolix were observed when co-administered with voriconazole (strong CYP3A inhibitor), fluconazole (moderate CYP3A inhibitor), or atorvastatin (weak CYP3A inhibitor). No clinically significant differences in the pharmacokinetics of midazolam (sensitive CYP3A substrate), rosuvastatin (BCRP substrate), or dabigatran etexilate (P-gp substrate) were observed upon co-administration with relugolix.

In Vitro Studies

- Cytochrome P450 (CYP) Enzymes: Relugolix is a substrate of CYP3A and CYP2C8. Relugolix is an inducer of CYP3A and CYP2B6, but not an inducer of CYP1A2. Relugolix is not an inhibitor of CYP1A2, CYP2B6, CYP2C8, CYP2C9, CYP2C19, CYP2D6, or CYP3A4.
- Transporter Systems: Relugolix is a substrate of P-gp, but not a substrate of BCRP. Relugolix is an inhibitor of BCRP and P-gp, but not an inhibitor of OATP1B1, OATP1B3, OATP2B1, OAT1, OAT3, OCT2, MATE1, MATE2-K, or BSEP.

13 NONCLINICAL TOXICOLOGY

13.1 Carcinogenesis, Mutagenesis, Impairment of Fertility

Carcinogenesis

Relugolix

Two-year carcinogenicity studies were conducted in mice at oral relugolix doses up to 100 mg/kg/day and in rats at doses up to 600 mg/kg/day. Relugolix was not carcinogenic in mice or rats at exposures up to approximately 142 or 423 times, respectively, the exposure in human females at the MRHD of 40 mg daily, based on AUC.

E2/NETA

Long-term continuous administration of natural and synthetic estrogens in certain animal species increases the frequency of carcinomas of the breast, uterus, cervix, vagina, testis, and liver.

Mutagenesis

Relugolix was not mutagenic in the in vitro bacterial reverse mutation (Ames) assay or clastogenic in the in vitro chromosomal aberration assay in Chinese hamster lung cells or the in vivo rat bone marrow micronucleus assay.

Impairment of Fertility

In a fertility study in rats, no effect on female fertility was observed at up to 1000 mg/kg/day (300 times the MRHD of 40 mg daily in women). In rats, the binding affinity of relugolix for GnRH receptors is greater than 1000-fold less than in humans, and this study represents an assessment of non-pharmacological targets of relugolix.

In human GnRH-receptor knock-in mice, administration of relugolix at oral doses of 100 mg/kg and above twice daily to female mice induced a constant diestrus phase and decreased ovarian and uterine weights, effects which were reversible following cessation of treatment. In male knock-in mice, oral administration of relugolix decreased prostate and seminal vesicle weights at doses 3 mg/kg and above twice daily for 28 days, effects which were reversible, except for testis weight, which did not fully recover within 28 days after drug withdrawal.

In a 39-week toxicology study in monkeys, a decrease in the frequency of menses was observed in female monkeys at 50 mg/kg/day (99 times the MRHD of 40 mg daily in women, based on AUC), which was partially reversed following a 13-week recovery period. There were no significant effects on male reproductive organs at oral relugolix doses up to 50 mg/kg/day (approximately 53 times the human exposure at a dose of 120 mg daily in men, based on AUC).

13.2 Animal Toxicology and/or Pharmacology

Phospholipidosis (intracellular phospholipid accumulation) was observed in multiple organs and tissues (e.g., liver, pancreas, spleen, kidney, lymph nodes, lung, bone marrow, GI tract or testes) after repeated oral administration of relugolix in rats and monkeys. In a rat 26-week toxicity study, phospholipidosis was observed at doses of 100 mg/kg (approximately 30 times the exposure at the MRHD of 40 mg daily in women based on AUC) and above. In a monkey 39-week toxicity study, this effect was observed at doses of 1.5 mg/kg (approximately equal to the MRHD) and above and demonstrated evidence of reversibility after cessation of treatment. The significance of this finding in humans is unknown.

14 CLINICAL STUDIES

14.1 Heavy Menstrual Bleeding Associated with Uterine Fibroids

The efficacy and safety of MYFEMBREE were evaluated in two replicate, 24-week, multinational, randomized, double-blind, placebo-controlled studies in a total of 768 premenopausal women with heavy menstrual bleeding associated with uterine fibroids in Study L1 (NCT03049735) and Study L2 (NCT03103087).

For study inclusion, women had to have uterine fibroids confirmed by ultrasound examination in which at least one fibroid met at least one of the following criteria:

- Subserosal, intramural, or < 50% intracavitary submucosal fibroid with a diameter ≥ 2 cm, or
- Multiple small fibroids with a total uterine volume of ≥ 130cm^3.

Women also had to have menstrual blood loss (MBL) volume of ≥ 80 mL per cycle for two menstrual cycles or ≥ 160 mL during one cycle quantified by the alkaline hematin method from menstrual products collected during baseline menstrual cycles to be included in the studies. Women with hemoglobin < 8.0 g/dL were excluded from the study. Iron therapy was required for women with hemoglobin ≥ 8 g/dL and ≤ 10 g/dL. Women were allowed, but not required, to take calcium and vitamin D during the study.

In Studies L1 and L2, women were randomized 1:1:1 to receive a once daily relugolix 40 mg tablet plus an over encapsulated tablet of E2 1 mg and NETA 0.5 mg (relugolix+E2/NETA), which is equivalent to 1 tablet of MYFEMBREE, for 24 weeks, placebo for 24 weeks, or relugolix 40 mg monotherapy for 12 weeks followed by MYFEMBREE for 12 weeks. Treatment was initiated within the first seven days after the onset of menses.

The primary endpoint was the proportion of women in the MYFEMBREE group compared with women in the placebo group, who achieved menstrual blood loss volume of < 80 mL and at least a 50% reduction from baseline MBL volume over the last 35 days of treatment, as measured by the alkaline hematin method. Key secondary endpoints were related to amenorrhea, MBL volume, and change in hemoglobin.

A total of 768 women were randomized and treated in Studies L1 and L2 (741 women in the efficacy population used for these studies). Of the 741 women, 247 received treatment with MYFEMBREE (122 and 125 in Studies L1 and L2, respectively), 252 received treatment with relugolix followed by MYFEMBREE (125 and 127 in Studies L1 and L2, respectively), and 242 received placebo (113 and 129 in Studies L1 and L2, respectively). The median age of women included in the efficacy analysis was 43 years (19 - 51 years), and mean body mass index was 31.6 kg/m^2. Approximately 53% of study participants were Black, 41% were White, and 6% were of other races. Across studies at baseline, mean (± standard deviation) MBL volume at baseline was 231 mL (± 156). Baseline uterine size in Studies L1 and L2 ranged from normal to greater than 28 weeks gestation size (47 - 2625 cm^3).

Menstrual Blood Loss

In both Study L1 and Study L2, a statistically higher proportion of women treated with MYFEMBREE achieved the primary endpoint of both an MBL volume of less than 80 mL and at least a 50% reduction from baseline in MBL volume over the last 35 days of treatment compared with placebo (Table 8).

Table 8: Proportion of Responders for Reduction in MBL Volume Over Last 35 days of Treatment in Women with Uterine Fibroids (Studies L1 and L2)
 | Study L1 |  | Study L2
 | MYFEMBREE (N = 122) | Placebo (N = 113) | MYFEMBREE (N = 125) | Placebo (N = 129)
Women with MBL Volume < 80 mL and ≥50% Reduction in MBL Volume from Baseline to the Last 35 Days of Treatment | 72.1% | 16.8% | 71.2% | 14.7%
Difference from placebo, % 95% CI p-value | 55.3% (44.2%, 65.6%) < 0.0001 |  | 56.5% (46.6%, 66.5%) < 0.0001
Abbreviations: CI = confidence interval.

Amenorrhea

In Studies L1 and L2, 50.0% and 50.4% of women treated with MYFEMBREE, respectively, achieved amenorrhea as compared to 6.2% and 3.1% treated with placebo, respectively, over the last 35 days of treatment.

Percent Change in MBL Volume

The mean MBL volumes in Studies L1 and L2 at baseline were 243.8 mL and 246.7 mL in the MYFEMBREE group and 223.2 mL and 211.8 mL in the placebo group, respectively. The mean reduction in MBL volume from baseline to Week 24 in the MYFEMBREE group was 82.0% in Study L1 and 84.3% in Study L2, which was greater than placebo (19.1% and 15.1%, respectively).

Reductions in MBL volume for MYFEMBREE and placebo groups are depicted in Figure 1.

Figure 1: Percent Change from Baseline in Menstrual Blood Loss Over 24 weeks

Study L1

Study L2

Hemoglobin Levels

For efficacy, a hemoglobin response was defined as a hemoglobin increase > 2 g/dL from baseline to Week 24 in the subgroup of women with anemia at baseline (hemoglobin ≤ 10.5 g/dL). A statistically higher proportion treated with MYFEMBREE compared with placebo had > 2 g/dL improvement in hemoglobin levels, see Table 9.

Table 9: Proportion of Women with Baseline Hgb ≤ 10.5 and > 2 g/dL Improvement in Hemoglobin Levels from Baseline at Week 24
 | Study L1 |  | Study L2
 | MYFEMBREE n=43 (N = 122) | Placebo n=29 (N = 113) | MYFEMBREE n=40 (N = 125) | Placebo n=53 (N = 129)
% at Week 24 | 44.2% | 17.2% | 55.0% | 5.7%
Difference from placebo, % 95% CI p-value | 26.9% (6.7%, 47.2%) 0.0177 |  | 49.3% (32.7%, 66.0%) <0.0001
Abbreviation: CI = confidence interval.
n = number of patients with Hgb ≤10.5 g/dL at baseline.
N = number of patients in each treatment group.

Recurrence of Heavy Menstrual Bleeding After Discontinuation of MYFEMBREE

In a randomized withdrawal study (L4), 229 women from the open label extension Study L3 were rerandomized to either continue blinded treatment with MYFEMBREE or withdrawal of therapy (placebo) for an additional 52 weeks. The median time to return to heavy menstrual bleeding among women randomized to placebo (treatment withdrawal) was 5.9 weeks.

14.2 Moderate to Severe Pain Associated with Endometriosis

The efficacy of MYFEMBREE was assessed in two 24-week, multinational, randomized, double-blind, placebo-controlled studies in pre-menopausal women with moderate to severe pain associated with endometriosis in Study S1 (NCT03204318) and Study S2 (NCT03204331).

In Studies S1 and S2, women with moderate to severe pain associated with endometriosis were randomized 1:1:1 to receive once daily treatment with a tablet of relugolix 40 mg plus an over encapsulated tablet of E2 1 mg and NETA 0.5 mg, (equivalent to one tablet of MYFEMBREE) for 24 weeks, placebo for 24 weeks, or relugolix 40 mg monotherapy for 12 weeks followed by MYFEMBREE for 12 weeks.

For study inclusion, women had to have endometriosis confirmed by direct visualization during surgery and/or histology in addition to pain associated with endometriosis during a placebo run-in period. Dysmenorrhea (DYS) and non-menstrual pelvic pain (NMPP) were assessed daily using an 11-point numerical rating scale (NRS) ranging from 0 (“no pain”) to 10 (“pain as bad as you can imagine”). Specifically, women had to have pain that met the following criteria:

- DYS NRS score ≥ 4.0 on at least 2 days AND
- Mean NMPP NRS score ≥ 2.5 or
  Mean NMPP NRS score ≥ 1.25 and NMPP NRS score ≥ 5.0 on at least 4 days

Studies S1 and S2 each had two co-primary endpoints. The first co-primary endpoint was a responder analysis where a responder was defined as a woman who achieved a reduction from baseline in dysmenorrhea (DYS) NRS of at least 2.8 points over the last 35 days of treatment, without an increase in analgesic use (nonsteroidal anti-inflammatory drug or opioid). The second co-primary endpoint was a responder analysis where a responder was defined as a woman who achieved a reduction from baseline in non-menstrual pelvic pain (NMPP) NRS score of at least 2.1 points over the last 35 days of treatment, without an increase in analgesic use (nonsteroidal anti-inflammatory drug or opioid) for pain associated with endometriosis.

In Study S1, a total of 424 women were included in the efficacy population (212 received MYFEMBREE; 212 received placebo). The median age of the efficacy population was 34 years and the mean body mass index was 26 kg/m^2. Approximately 92% were White, 6% were Black, and 7% were of Hispanic or Latino descent. A total of 19% were from the United States and/or Canada. At baseline, 29% of women used an opioid rescue analgesic for moderate to severe pain associated with endometriosis.

In Study S2, a total of 405 women were included in the efficacy population (205 received MYFEMBREE; 200 received placebo). The median age of the efficacy population was 34 years and the mean body mass index was 26 kg/m^2. Approximately 90% were White, 6% were Black, and 17% were of Hispanic or Latino descent. A total of 24% were from United States and none were from Canada. At baseline, 48% of women used an opioid rescue analgesic for moderate to severe pain associated with endometriosis.

The results for the co-primary efficacy endpoints as assessed at Week 24 are shown below in Table 10.

Table 10: Proportion of Dysmenorrhea and Non-Menstrual Pelvic Pain Responders at Week 24
 | Study S1 |  | Study S2
 | MYFEMBREE (N = 212) | Placebo (N = 212) | MYFEMBREE (N = 205) | Placebo (N = 200)
Dysmenorrhea | 74.5% | 26.9% | 75.1% | 30.5%
Difference from placebo (95% CI) p-value | 47.6% (39.3%, 56.0%) ≤ 0.0001 | - | 44.6% (35.9%, 53.3%) ≤ 0.0001 | -
Non-menstrual pelvic pain | 58.5% | 39.6% | 65.9% | 42.5%
Difference from placebo (95% CI) * p-value | 18.9% (9.5%, 28.2%) ≤ 0.0001 | - | 23.4% (13.9%, 32.8%) ≤ 0.0001 | -
Abbreviations: CI = confidence interval.
Responders are women with a reduction from baseline of at least 2.8 points on the NRS for dysmenorrhea or at least 2.1 points on the NRS for non-menstrual pelvic pain and no increase in analgesic use over the last 35 days of treatment.

Key secondary efficacy endpoints included changes from baseline in the DYS NRS scores, NMPP NRS scores, Endometriosis Health Profile-30 (EHP-30) pain domain scores, dyspareunia NRS scores, and opioid use.

Reduction in DYS and NMPP NRS Scores

Women treated with MYFEMBREE had a greater reduction in DYS and NMPP NRS scores as compared to placebo from baseline to Week 24 in both Studies S1 and S2 (Figure 2 and Figure 3).

Figure 2: Mean DYS NRS Scores in Study S1 and Study S2 over 24 Weeks

Study S1

Study S2

Figure 3: Mean NMPP NRS Scores in Study S1 and Study S2 over 24 Weeks

Study S1

Study S2

Reduction in EHP-30 Pain Domain Scores

The impact of moderate to severe pain associated with endometriosis was evaluated using the pain domain from the Endometriosis Health Profile-30 (EHP-30), where the domain score (normalized) ranges from 0 to 100 with a higher score representing greater impact of pain on activities.

Women taking MYFEMBREE reported an improvement from baseline in EHP-30 pain domain score compared to placebo at Week 24 in both Studies S1 and S2 (Study S1: -33.8 vs. -18.7 with a treatment difference of -15.1 [95% CI: -19.7, -10.5] and Study S2: -32.2 vs. -20.0 with a treatment difference of -12.3 [95% CI: -16.7, -7.8]). Least squares mean changes in EHP-30 pain domain scores over time are shown in Figure 4.

Figure 4: Mean Change in EHP-30 Pain Domain Scores in Studies S1 and S2 over 24 Weeks

Study S1

Study S2

Reduction in Dyspareunia

Dyspareunia associated with endometriosis was evaluated in a subgroup of women who engaged in sexual activity with vaginal intercourse at baseline and during treatment (68% of enrolled women). Dyspareunia (pain during sexual intercourse) was assessed daily using an 11-point NRS ranging from 0 (“no pain”) to 10 (“pain as bad as you can imagine”). In Studies S1 and S2, women treated with MYFEMBREE had a greater reduction in dyspareunia from baseline to Week 24 compared with placebo [LS mean change in Study S1: -2.4 vs. -1.7, with a treatment difference of -0.7 (95% CI: -1.3, -0.1); in Study S2: -2.4 vs. -1.9, with a treatment difference of -0.5 (95% CI: -1.0, 0.0)].

Use of Opioid Rescue Analgesics

The opioid analgesics used in the studies were tramadol 50 mg, codeine 30 mg, tramadol/acetaminophen (TRM/APAP) 37.5/325 mg, codeine/APAP at strengths of 15/500 mg, 30/300 mg, and 30/500 mg, and hydrocodone/acetaminophen 5/325 mg. The opioid rescue analgesics used at baseline, Month 3, and Month 6 are shown in Table 11.

The clinical relevance of these data has not been demonstrated.

Table 11: Opioid Rescue Analgesic Use in Studies S1 and S2
 | Study S1 |  | Study S2
 | MYFEMBREE (N = 212) | Placebo (N = 212) | MYFEMBREE (N = 205) | Placebo (N = 200)
Tablets per month at baseline Mean (SD) Median (Min, Max) | 9.1 (12.36) 4.2 (0.6, 60.7) | 11.7 (11.95) 7.2 (0.5, 54.6) | 9.0 (13.51) 5.6 (0.7, 106.9) | 10.0 (12.82) 6.1 (0.4, 86.3)
Tablets per month at Month 3 Mean (SD) Median (Min, Max) | 3.9 (7.98) 0.0 (0.0, 32.0) | 8.2 (11.48) 3.2 (0.0, 40.8) | 3.4 (8.26) 0.0 (0.0, 57.6) | 7.5 (23.49) 2.4 (0.0, 215.2)
Tablets per month at Month 6 Mean (SD) Median (Min, Max) | 4.8 (10.38) 0.0 (0.0, 45.4) | 10.7 (28.93) 3.2 (0.0, 40.8) | 2.4 (5.02) 0.0 (0.0, 28.0) | 5.6 (14.16) 1.2 (0.0, 120.8)
Number and % of subjects on any dose of opioid rescue at baseline who were off opioid at Month 3* | 33/64 (51.6%) | 10/56 (17.9%) | 46/100 (46.0%) | 27/94 (28.7%)
Number and % of subjects on any dose of opioid rescue at baseline who were off opioid at Month 6* | 39/64 (60.9%) | 18/56 (32.1%) | 65/100 (65.0%) | 38/94 (40.4%)
Number and % of subjects not on opioid rescue at baseline who were on opioid at Month 3# | 4/148 (2.7%) | 10/156 (6.4%) | 6/105 (5.7%) | 15/106 (14.2%)
Number and % of subjects not on any dose of opioid rescue at baseline who were on opioid at Month 6# | 5/148 (3.4%) | 12/156 (7.7%) | 2/105 (1.9%) | 12/106 (11.3%)
Max = maximum; Min = minimum; SD = standard deviation; monthly tablets calculations are both on 28-day interval.
* = denominator is the number of subjects on opioid rescue analgesics at baseline.
# = denominator is the number of subjects off opioid rescue analgesics at baseline.

16 HOW SUPPLIED/STORAGE AND HANDLING

16.1 How Supplied

MYFEMBREE film-coated tablets contain relugolix 40 mg, estradiol (E2) 1 mg, and norethindrone acetate (NETA) 0.5 mg. The tablets are light yellow to yellow, round film-coated tablet with “MVT” on one side and “415” on the other side.

MYFEMBREE is supplied in a white, opaque, high-density polyethylene bottle containing 28 tablets with desiccant and closed with an induction-sealed child-resistant cap (NDC Code 72974-415-01).

16.2 Storage and Handling

Store at 15ºC to 30ºC (59ºF to 86ºF).

Dispose unused medication via a take-back option if available. Otherwise, follow FDA instructions for disposing medication in the household trash, www.fda.gov/drugdisposal. Do NOT flush down the toilet.

17 PATIENT COUNSELING INFORMATION

Advise the patient to read the FDA-approved patient labeling (Patient Information).

Thromboembolic Disorders and Vascular Events

Advise patients that use of estrogen and progestin combinations may increase the risk of venous and arterial thrombotic/thromboembolic events, especially in women at high risk for these events [see Boxed Warning, Contraindications (4) and Warnings and Precautions (5.1)].

Bone Loss

Advise patients about the risk of bone loss. Advise patients that supplementary calcium and vitamin D may be beneficial if dietary intake of calcium and vitamin D is not adequate. Advise women that oral iron supplementation should not be taken at the same time as calcium and vitamin D [see Warnings and Precautions (5.2) and Adverse Reactions (6.1)].

Suicidal Ideation and Mood Disorders (Including Depression)

Advise patients that depression, mood disorders, and suicidal ideation may occur with MYFEMBREE use. Instruct women with new onset or worsening depression, anxiety, or other mood changes to promptly seek medical attention [see Warnings and Precautions (5.4) and Adverse Reactions (6.1)].

Hepatic Impairment and Transaminase Elevations

Advise women to promptly seek medical attention in case of signs or symptoms that may reflect liver injury, such as jaundice [see Warnings and Precautions (5.5)].

Change in Menstrual Bleeding Pattern and Reduced Ability to Recognize Pregnancy

Advise patients that MYFEMBREE may delay the recognition of pregnancy because it may reduce the duration and amount of menstrual bleeding. Advise patients to use effective non-hormonal contraception while taking MYFEMBREE and to discontinue MYFEMBREE if pregnancy is diagnosed [see Warnings and Precautions (5.8)]. Advise pregnant patients that there is a pregnancy registry that monitors pregnancy outcomes in women exposed to MYFEMBREE during pregnancy [see Use in Specific Populations (8.1, 8.3)].

Alopecia

Advise women with uterine fibroids that alopecia, hair loss, and hair thinning in no specific pattern may occur with MYFEMBREE. Advise these women that hair loss and hair thinning may not resolve completely after stopping MYFEMBREE. Advise these women to contact their healthcare provider if they have concerns about changes to their hair [see Warnings and Precautions (5.11) and Adverse Reactions (6.1)].

Females of Reproductive Potential

Advise women to use effective non-hormonal contraception while taking MYFEMBREE and for one week after discontinuing treatment and to discontinue MYFEMBREE if pregnancy is confirmed. Advise pregnant patients that there is a pregnancy registry that monitors pregnancy outcomes in women exposed to MYFEMBREE during pregnancy [see Use in Specific Populations (8.1, 8.3)].

Drug Interactions

Advise women to report their use of any other prescription or nonprescription medications or dietary supplements. Co-administration with certain drugs may decrease the therapeutic effects of MYFEMBREE [see Drug Interactions (7.1)].

Administration Instructions

- Advise women to begin taking MYFEMBREE as soon as possible after the start of menses but no later than 7 days after menses has started [see Dosage and Administration (2.2)].
- Advise women to take any missed dose of MYFEMBREE as soon as possible the same day and then resume regular dosing the next day at the usual time [see Dosage and Administration (2.3)].
- Advise women taking oral P-gp inhibitors to take MYFEMBREE first and separate dosing by at least 6 hours [see Dosage and Administration (2.4)].

Manufactured by Patheon Inc., 2100 Syntex Court, Mississauga, Ontario L5N 7K9, Canada

Distributed by: Sumitomo Pharma America, Inc., 84 Waterford Drive, Marlborough, MA 01752

214846 MS 007

PATIENT INFORMATION
MYFEMBREE® (mye fem' brē)
(relugolix, estradiol and norethindrone acetate)
tablets, for oral use

What is the most important information I should know about MYFEMBREE?
MYFEMBREE may cause serious side effects, including:

- cardiovascular conditions
  - MYFEMBREE may increase your chances of heart attack, stroke, or blood clots, especially if you are over 35 years of age, smoke, and have uncontrolled high blood pressure. Stop taking MYFEMBREE and call your healthcare provider right away or go to the nearest hospital emergency room right away if you have:
    - leg pain or swelling that will not go away
    - sudden shortness of breath
    - double vision, bulging of the eyes, or sudden blindness, partial or complete
    - pain or pressure in your chest, arm, or jaw
    - sudden, severe headache unlike your usual headaches
    - weakness or numbness in an arm or leg, or trouble speaking
- bone loss (decreased bone mineral density)
  - While you are taking MYFEMBREE, your estrogen levels may be low. Low estrogen levels can lead to bone mineral density loss.
  - If you have bone loss on MYFEMBREE, your bone density may improve after you stop taking MYFEMBREE, but complete recovery may not occur. It is unknown if these bone changes could increase your risk for broken bones as you age. For this reason, you should not take MYFEMBREE for more than 24 months.
  - Your healthcare provider may order an X-ray test called a DXA scan to check your bone mineral density when you start taking MYFEMBREE and periodically after you start if you have uterine fibroids or annually if you have pain associated with endometriosis.
  - Your healthcare provider may advise you to take vitamin D and/or calcium supplements as part of a healthy lifestyle that promotes bone health. If you are also advised to take iron supplements, they should be taken at least two hours apart from your vitamin D or calcium supplements.
- effects on pregnancy
  - Do not take MYFEMBREE if you are trying to become pregnant or are pregnant. It may increase the risk of early pregnancy loss.
  - If you think you are pregnant, stop taking MYFEMBREE right away and call your healthcare provider.
    - If you become pregnant while taking MYFEMBREE, you are encouraged to enroll in the Pregnancy Registry. The purpose of the pregnancy registry is to collect information about the health of you and your baby. Talk to your healthcare provider or call 1-(855) 428-0707.
  - MYFEMBREE can decrease your menstrual bleeding or result in no menstrual bleeding at all, making it hard to know if you are pregnant. Watch for other signs of pregnancy such as breast tenderness, weight gain and nausea.
  - MYFEMBREE does not prevent pregnancy. You will need to use effective methods of birth control while taking MYFEMBREE and for 1 week after you stop taking MYFEMBREE. Examples of effective methods can include condoms or spermicide, which do not contain hormones.
  - Do not take hormonal birth control such as birth control pills because they may increase your side effects and MYFEMBREE may not work as well.
    Talk to your healthcare provider about which birth control to use during treatment with MYFEMBREE. Your healthcare provider may change the birth control you were on before you start taking MYFEMBREE.

What is MYFEMBREE?

- MYFEMBREE is a prescription medicine used in premenopausal women (before “change of life” or menopause) to
  - control heavy menstrual bleeding due to uterine fibroids or
  - manage moderate to severe pain associated with endometriosis.
- MYFEMBREE contains relugolix, which reduces the amount of estrogen (and other hormones) produced by ovaries, estradiol (an estrogen) which may reduce the risk of bone loss, and norethindrone acetate (a progestin) which is necessary when women with a uterus (womb) take estrogen.
- It is not known if MYFEMBREE is safe to use more than 24 months due to the risk of continued bone loss that may not be reversible.
- It is not known if MYFEMBREE is safe and effective in children under 18 years of age.

Do not take MYFEMBREE if you:

- have or have had:
  - blood clots in your legs (deep vein thrombosis), lungs (pulmonary embolism), or eyes (retinal thrombosis)
  - stroke or heart attack
  - a problem that makes your blood clot more than normal
  - blood circulation disorders
  - certain heart valve problems or heart rhythm abnormalities that can cause blood clots to form in the heart
  - high blood pressure not well controlled by medicine
  - diabetes with kidney, eye, nerve, or blood vessel damage
  - certain kinds of severe migraine headaches with aura, numbness, weakness or changes in vision or migraine headaches if you are over age 35
  - breast cancer or any cancer that is sensitive to female hormones
  - osteoporosis
  - vaginal bleeding that has not been diagnosed. Your healthcare provider should check any unexplained vaginal bleeding to find out the cause.
  - liver problems including liver disease
- smoke and are over 35 years old
- have had a serious allergic reaction with symptoms that included swelling of your face, lips, mouth or tongue, trouble breathing, skin rashes, redness, or swelling or an allergic reaction to relugolix, estradiol, norethindrone or any of the ingredients in MYFEMBREE. See the end of this Patient Package Insert for a complete list of ingredients in MYFEMBREE.

Before you take MYFEMBREE, tell your healthcare provider about all of your medical conditions including if you:

- have or have had:
  - broken bones or other conditions that may cause bone problems.
  - depression, mood swings, or suicidal thoughts or behavior.
  - yellowing of the skin or eyes (jaundice) or jaundice caused by pregnancy (cholestasis of pregnancy).
- are scheduled for surgery or will be on bed rest. MYFEMBREE may increase your risk of blood clots after surgery. Your healthcare provider may advise you to stop taking MYFEMBREE before you have surgery. Talk to your healthcare provider about when to stop MYFEMBREE before surgery and when to restart MYFEMBREE after surgery.
- are pregnant or think you may be pregnant or just had a baby.
- are breastfeeding. MYFEMBREE may pass into your breast milk. Talk to your healthcare provider about the best way to feed your baby if you take MYFEMBREE.

Tell your healthcare provider about all the medicines you take, including prescription, over-the-counter medicines, vitamins, and herbal supplements.
Women on thyroid or cortisol replacement therapy may need increased doses of the hormone.
Know the medicines you take. Keep a list of your medicines with you to show to your healthcare provider and pharmacist when you get a new medicine.

How should I take MYFEMBREE?

- Take MYFEMBREE exactly as your healthcare provider tells you to take it.
- Take MYFEMBREE 1 time each day at about the same time with or without food.
- If you have to take oral P-gp inhibitors, take MYFEMBREE first and wait at least 6 hours before taking the P-gp inhibitor. Ask your healthcare provider if you are not sure if you are taking this type of medicine.
- Your healthcare provider may give you a pregnancy test before you start taking MYFEMBREE.
- You should begin MYFEMBREE as soon as possible after your period begins, but no later than 7 days after your period has started. If you start MYFEMBREE on another day, your period may become heavy or irregular for the first month after starting treatment, but bleeding should decrease after this time.
- If you take too much MYFEMBREE, call your healthcare provider or go to the nearest hospital emergency room right away.
- If you miss a dose, take the missed dose as soon as you remember on that day, and then take MYFEMBREE at the usual time the next day.
- Do not take 2 doses at once to make up for the missed dose. If you do not remember until you are due for MYFEMBREE on the next day, do not make up for the missed dose.

What are the possible side effects of MYFEMBREE?
MYFEMBREE may cause serious side effects including:

- See “What is the most important information I should know about MYFEMBREE?”
- suicidal thoughts, suicidal behavior, and worsening of mood. Call your healthcare provider or get emergency medical help right away if you have any of these symptoms, especially if they are new, worse, or bother you:
  - thoughts about suicide or dying
  - attempts to commit suicide
  - new or worse depression
  - new or worse anxiety
  - other unusual changes in behavior or mood
    Pay attention to any changes, especially sudden changes in your mood, behaviors, thoughts, or feelings.
- abnormal liver tests. Call your healthcare provider right away if you have any of these signs and symptoms of liver problems:
  - jaundice
  - dark, amber-colored urine
  - feeling tired (fatigue or exhaustion)
  - nausea and vomiting
  - generalized swelling
  - right upper stomach area (abdomen) pain
  - bruising easily
- gallbladder problems (cholestasis), especially if you had cholestasis of pregnancy.
- high blood pressure. See your healthcare provider to check your blood pressure regularly.
- uterine fibroid prolapse or expulsion. Fibroids can come out completely or partially through the vagina. Call your healthcare provider right away if you have increased bleeding from the vagina, which can be serious, or cramping, while taking MYFEMBREE.
- hair loss (alopecia). In women with uterine fibroids, hair loss and hair thinning can happen while taking MYFEMBREE. It is not known if this hair loss or hair thinning stops after you stop taking MYFEMBREE or is reversible. Talk to your healthcare provider if this is a concern for you.
- increases in the blood sugar, cholesterol and fat (triglycerides) levels in your blood.
- changes in laboratory tests including thyroid, steroid, hormone, cholesterol, and blood clotting tests.

The most common side effects of MYFEMBREE in women that have heavy bleeding with uterine fibroids include:

- hot flushes
- increased sweating
- night sweats
- abnormal vaginal bleeding (bleeding that lasts too long, that is too much, or is unexpected)
- hair loss or hair thinning
- decreased interest in sex

The most common side effects of MYFEMBREE in women that have moderate to severe pain with endometriosis include:

- headache
- hot flushes, sweating, or night sweats
- mood changes including worsening depression
- abnormal vaginal bleeding (bleeding that lasts too long, that is too much, or is unexpected)
- nausea
- toothache
- back pain
- decreased interest in sex
- joint pain
- tiredness
- dizziness

These are not all the possible side effects of MYFEMBREE. Call your doctor for medical advice about side effects. You may report side effects to FDA at 1-800-FDA-1088.

How should I store MYFEMBREE?

- Store MYFEMBREE between 59°F to 86°F (15°C to 30°C).
- Dispose of unused medicines through community take-back disposal programs when available. If no community take-back disposal program is available go to www.fda.gov/drugdisposal for information on how to dispose of MYFEMBREE the right way.
- Do not flush MYFEMBREE down the toilet.
- Do not keep medicine that is out of date or that you no longer need.
- Keep MYFEMBREE and all medicines out of the reach of children.

General information about the safe and effective use of MYFEMBREE.
Medicines are sometimes prescribed for purposes other than those listed in a Patient Information leaflet. Do not use MYFEMBREE for a condition for which it was not prescribed. Do not give MYFEMBREE to other people, even if they have the same symptoms that you have. It may harm them. You can ask your healthcare provider or pharmacist for information about MYFEMBREE that is written for health professionals.

What are the ingredients of MYFEMBREE?
Active ingredient: relugolix, estradiol, and norethindrone acetate
Inactive ingredients: lactose monohydrate, mannitol, sodium starch glycolate, hydroxypropyl cellulose, magnesium stearate, hypromellose, titanium dioxide, triacetin, iron oxide yellow.
Manufactured by: Patheon Inc., Mississauga, Ontario, Canada
Manufactured for: Sumitomo Pharma America, Inc., Marlborough, MA 01752
For more information, call Sumitomo Pharma America, Inc. at 1-833-696-8268 or go to www.MYFEMBREE.com

This Patient Package Insert has been approved by the U.S. Food and Drug Administration

Approved: 08/2025

214846 MS 007

PRINCIPAL DISPLAY PANEL - 28 Tablet Bottle Label

NDC 72974-415-01
Rx only

Myfembree®

(relugolix, estradiol, and
norethindrone acetate) tablets
40 mg, 1 mg, 0.5 mg

28 tablets